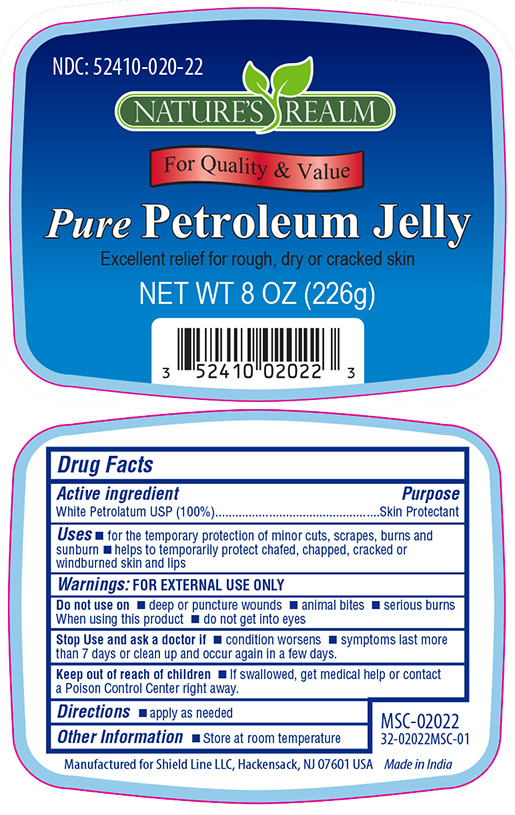 DRUG LABEL: PURE PETROLEUM
NDC: 52410-0202 | Form: JELLY
Manufacturer: Shield Line LLC
Category: otc | Type: HUMAN OTC DRUG LABEL
Date: 20210224

ACTIVE INGREDIENTS: PETROLATUM 100 g/100 g
INACTIVE INGREDIENTS: WATER

Active Ingredient

White Petrolatum USP (100%)

Purpose

Skin Protectant

Uses

- for the temporary protection of minor cuts, scrapes, burns and sunburn
- helps to temporarily protect chafed , chapped , cracked or windburned skin and lips

Warnings: FOR EXTERNAL USE ONLY

Do not use on

- deep or puncture wounds
- animal bites
- serious burns

When using this product

- do not get into eyes

Stop Use and ask a doctor if

- condition worsens
- symptoms last more than 7 days or clean up and occur again in a few days

Keep out of reach of childen

- if swalloed , get medical help or contact a Proison Control Center right away

Directions

- apply as needed

Other Information

- Store at room temperature

Inactive Ingradients

None